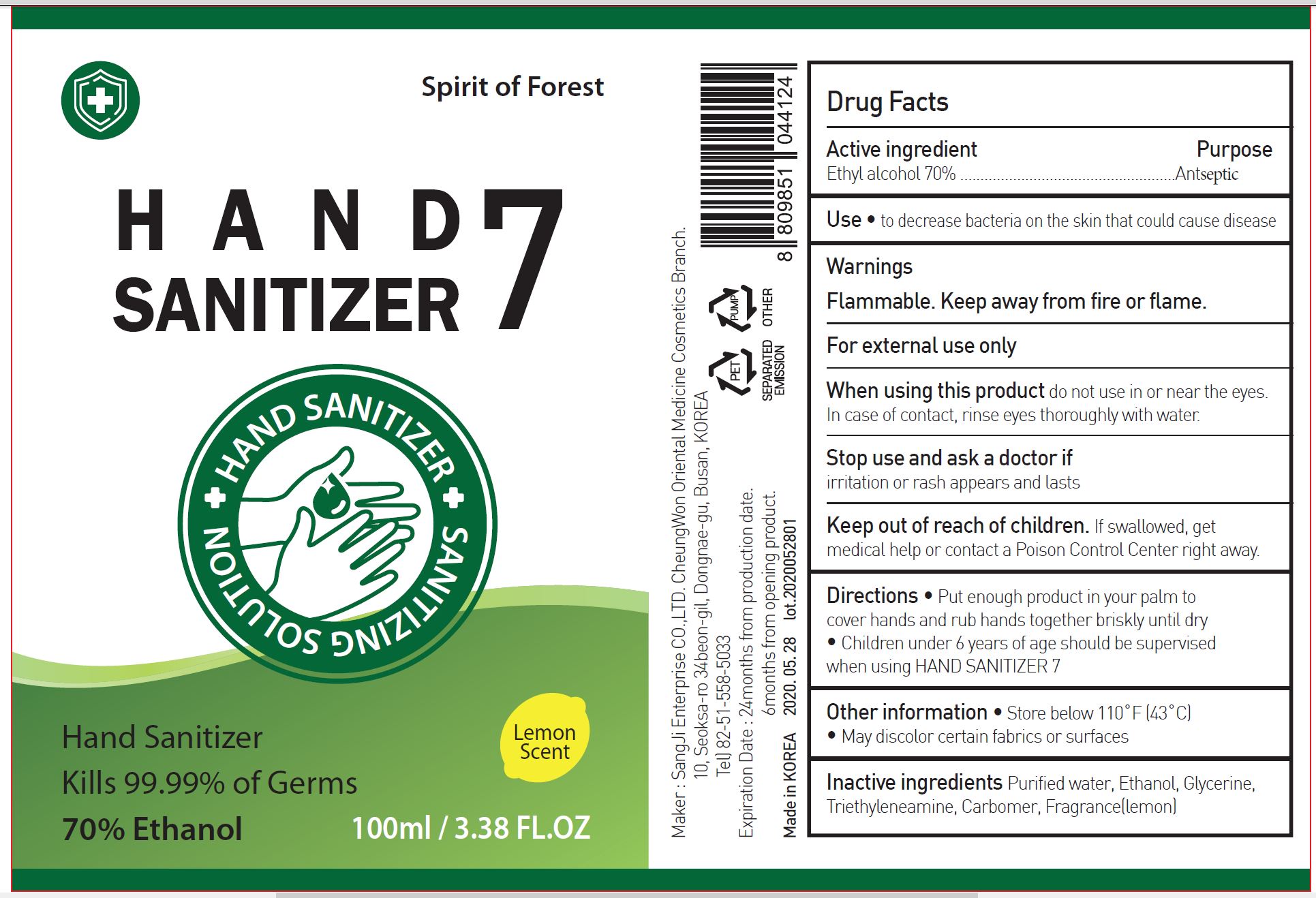 DRUG LABEL: HAND SANITIZER 7
NDC: 75695-0004 | Form: GEL
Manufacturer: Sangji Enterprise Co LTD Cheongwon Oriental Medical Cosmetic Branch
Category: otc | Type: HUMAN OTC DRUG LABEL
Date: 20200606

ACTIVE INGREDIENTS: ALCOHOL 70 mL/100 mL
INACTIVE INGREDIENTS: TROLAMINE; WATER; CARBOMER 940; GLYCERIN

Drug Facts

ACTIVE INGREDIENT

alcohol

PURPOSE

to decrease bacteria on the skin that could cause disease

KEEP OUT OF REACH OF THE CHILDREN

INDICATIONS AND USAGE

take appropriate amount on the hand, rub and dry well

WARNINGS

■ Flammable. Keep away from fire or flame.

■ For external use only.

■ Do not use in eyes.

■ lf swallowed, get medical help promptly.

■ Stop use, ask doctor lf irritation occurs.

■ Keep out of reach of children.

DOSAGE AND ADMINISTRATION

for external use only

INACTIVE INGREDIENT

Purified water, Ethanol, Glycerine, Triethyleneamine, Carbomer, Fragrance(lemon)